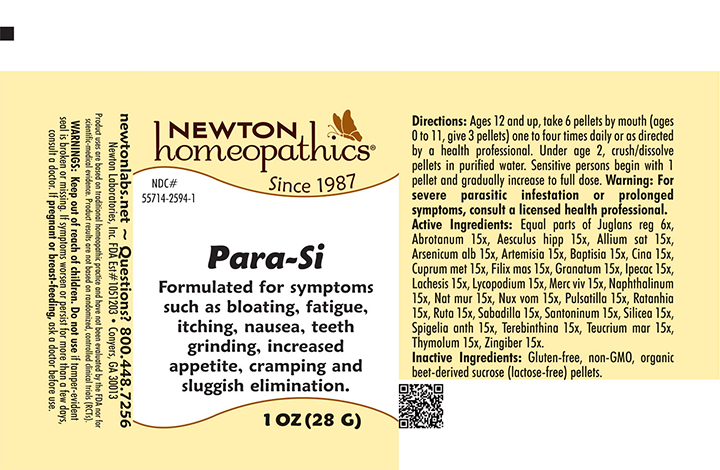 DRUG LABEL: Para-Si
NDC: 55714-2594 | Form: PELLET
Manufacturer: Newton Laboratories, Inc.
Category: homeopathic | Type: HUMAN OTC DRUG LABEL
Date: 20241126

ACTIVE INGREDIENTS: JUGLANS REGIA LEAF 6 [hp_X]/1 g; SPIGELIA ANTHELMIA 15 [hp_X]/1 g; THYMOL 15 [hp_X]/1 g; GARLIC 15 [hp_X]/1 g; ARSENIC TRIOXIDE 15 [hp_X]/1 g; BAPTISIA TINCTORIA ROOT 15 [hp_X]/1 g; ARTEMISIA CINA PRE-FLOWERING TOP 15 [hp_X]/1 g; COPPER 15 [hp_X]/1 g; DRYOPTERIS FILIX-MAS ROOT 15 [hp_X]/1 g; PUNICA GRANATUM ROOT BARK 15 [hp_X]/1 g; MERCURY 15 [hp_X]/1 g; IPECAC 15 [hp_X]/1 g; LACHESIS MUTA VENOM 15 [hp_X]/1 g; LYCOPODIUM CLAVATUM SPORE 15 [hp_X]/1 g; ARTEMISIA ABROTANUM FLOWERING TOP 15 [hp_X]/1 g; ANEMONE PULSATILLA 15 [hp_X]/1 g; NAPHTHALENE 15 [hp_X]/1 g; SODIUM CHLORIDE 15 [hp_X]/1 g; STRYCHNOS NUX-VOMICA SEED 15 [hp_X]/1 g; KRAMERIA LAPPACEA ROOT 15 [hp_X]/1 g; RUTA GRAVEOLENS FLOWERING TOP 15 [hp_X]/1 g; SCHOENOCAULON OFFICINALE SEED 15 [hp_X]/1 g; SANTONIN 15 [hp_X]/1 g; HORSE CHESTNUT 15 [hp_X]/1 g; SILICON DIOXIDE 15 [hp_X]/1 g; TURPENTINE OIL 15 [hp_X]/1 g; GINGER 15 [hp_X]/1 g; TEUCRIUM MARUM 15 [hp_X]/1 g; ARTEMISIA VULGARIS ROOT 15 [hp_X]/1 g
INACTIVE INGREDIENTS: SUCROSE

Para-Si 2594P

INDICATIONS & USAGE SECTION

Formulated for symptoms such as bloating, fatigue, itching, nausea, teeth grinding, increased appetite, cramping and sluggish elimination.

DOSAGE & ADMINISTRATION SECTION

Directions: Ages 12 and up, take 6 pellets by mouth (ages 0 to 11, give 3 pellets) one to four times daily or as directed by a health professional. Under age 2, crush/dissolve pellets in purified water. Sensitive persons begin with 1 pellet and gradually increase to full dose. Warning: For severe parasitic infestation or prolonged symptoms, consult a licensed health professional.

OTC - ACTIVE INGREDIENT SECTION

Equal parts of Juglans reg 6x, Abrotanum 15x, Aesculus hipp 15x, Allium sat 15x, Arsenicum alb 15x, Artemisia 15x, Baptisia 15x, Cina 15x, Cuprum met 15x, Filix mas 15x, Granatum 15x, Ipecac 15x, Lachesis 15x, Lycopodium 15x, Merc viv 15x, Naphthalinum 15x, Nat mur 15x, Nux vom 15x, Pulsatilla 15x, Ratanhia 15x, Ruta 15x, Sabadilla 15x, Santoninum 15x, Silicea 15x, Spigelia anth 15x, Terebinthina 15x, Teucrium mar 15x, Thymolum 15x, Zingiber 15x.

OTC - PURPOSE SECTION

Formulated for symptoms such as bloating, fatigue, itching, nausea, teeth grinding, increased appetite, cramping and sluggish elimination.

INACTIVE INGREDIENT SECTION

Inactive Ingredients: Gluten-free, non-GMO, organic beet-derived sucrose (lactose-free) pellets.

QUESTIONS SECTION

newtonlabs.net – Questions? 800.448.7256

Newton Laboratories, Inc. FDA Est # 1051203 - Conyers, GA 30013

WARNINGS SECTION

WARNINGS: Keep out of reach of children. Do not use if tamper-evident seal is broken or missing. If symptoms worsen or persist for more than a few days, consult a doctor. If pregnant or breast-feeding, ask a doctor before use.

OTC - PREGNANCY OR BREAST FEEDING SECTION

If pregnant or breast-feeding, ask a doctor before use.

OTC - KEEP OUT OF REACH OF CHILDREN SECTION

Keep out of reach of children.